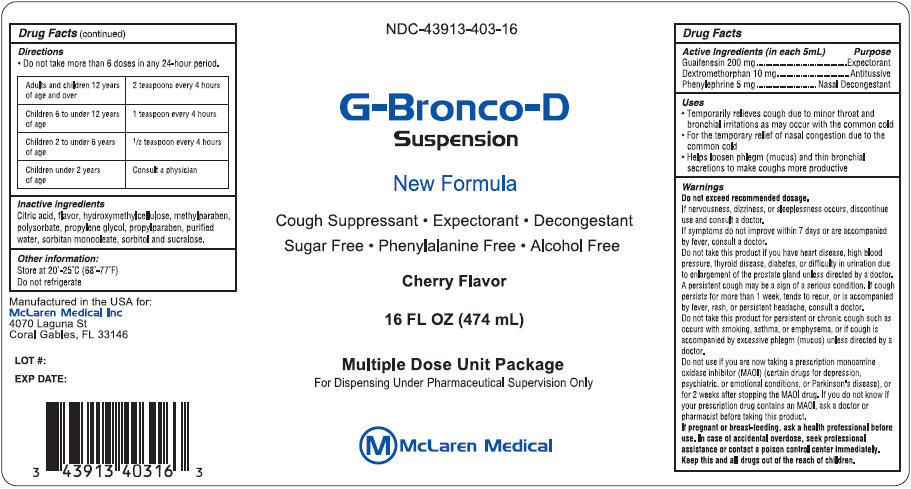 DRUG LABEL: G-BRONCO-D
NDC: 43913-403 | Form: SUSPENSION
Manufacturer: MCLAREN MEDICAL INC
Category: otc | Type: HUMAN OTC DRUG LABEL
Date: 20150629

ACTIVE INGREDIENTS: GUAIFENESIN 200 mg/5 mL; DEXTROMETHORPHAN HYDROBROMIDE 10 mg/5 mL; PHENYLEPHRINE HYDROCHLORIDE 5 mg/5 mL
INACTIVE INGREDIENTS: CITRIC ACID MONOHYDRATE; HYDROXYMETHYL CELLULOSE; METHYLPARABEN; POLYSORBATE 20; PROPYLENE GLYCOL; PROPYLPARABEN; WATER; SORBITAN MONOOLEATE; SORBITOL; SUCRALOSE

G-BRONCO-D

Drug Facts

ACTIVE INGREDIENT

Active Ingredients (in each 5mL) | Purpose
Guaifenesin 200 mg | Expectorant
Dextromethorphan 10 mg | Antitussive
Phenylephrine 5 mg | Nasal Decongestant

Uses

- Temporarily relieves cough due to minor throat and bronchial irritations as may occur with the common cold
- For the temporary relief of nasal congestion due to the common cold
- Helps loosen phlegm (mucus) and thin bronchial secretions to make coughs more productive

Warnings

Do not exceed recommended dosage.

STOP USE

If nervousness, dizziness, or sleeplessness occurs, discontinue use and consult a doctor.

ASK DOCTOR

If symptoms do not improve within 7 days or are accompanied by fever, consult a doctor.

DO NOT USE

Do not take this product if you have heart disease, high blood pressure, thyroid disease, diabetes, or difficulty in urination due to enlargement of the prostate gland unless directed by a doctor.

ASK DOCTOR

A persistent cough may be a sign of a serious condition. If cough persists for more than 1 week, tends to recur, or is accompanied by fever, rash, or persistent headache, consult a doctor.

DO NOT USE

Do not take this product for persistent or chronic cough such as occurs with smoking, asthma, or emphysema, or if cough is accompanied by excessive phlegm (mucus) unless directed by a doctor.

Do not use if you are now taking a prescription monoamine oxidase inhibitor (MAOI) (certain drugs for depression, psychiatric, or emotional conditions, or Parkinson's disease), or for 2 weeks after stopping the MAOI drug. If you do not know if your prescription drug contains an MAOI, ask a doctor or pharmacist before taking this product.

PREGNANCY OR BREAST FEEDING

If pregnant or breast-feeding, ask a health professional before use. In case of accidental overdose, seek professional assistance or contact a poison control center immediately.

KEEP OUT OF REACH OF CHILDREN

Keep this and all drugs out of the reach of children.

Directions

- Do not take more than 6 doses in any 24-hour period.

Adults and children 12 years of age and over | 2 teaspoons every 4 hours
Children 6 to under 12 years of age | 1 teaspoon every 4 hours
Children 2 to under 6 years of age | ½ teaspoon every 4 hours
Children under 2 years of age | Consult a physician

Inactive ingredients

Citric acid, flavor, hydroxymethylcellulose, methylparaben, polysorbate, propylene glycol, propylparaben, purified water, sorbitan monooleate, sorbitol and sucralose.

Other information

Store at 20°-25°C (68°-77°F)

Do not refrigerate

PRINCIPAL DISPLAY PANEL - 474 mL Bottle Label

NDC-43913-403-16

G-Bronco-D
Suspension

New Formula

Cough Suppressant • Expectorant • Decongestant
Sugar Free • Phenylalanine Free • Alcohol Free

Cherry Flavor

16 FL OZ (474 mL)

Multiple Dose Unit Package
For Dispensing Under Pharmaceutical Supervision Only

McLaren Medical